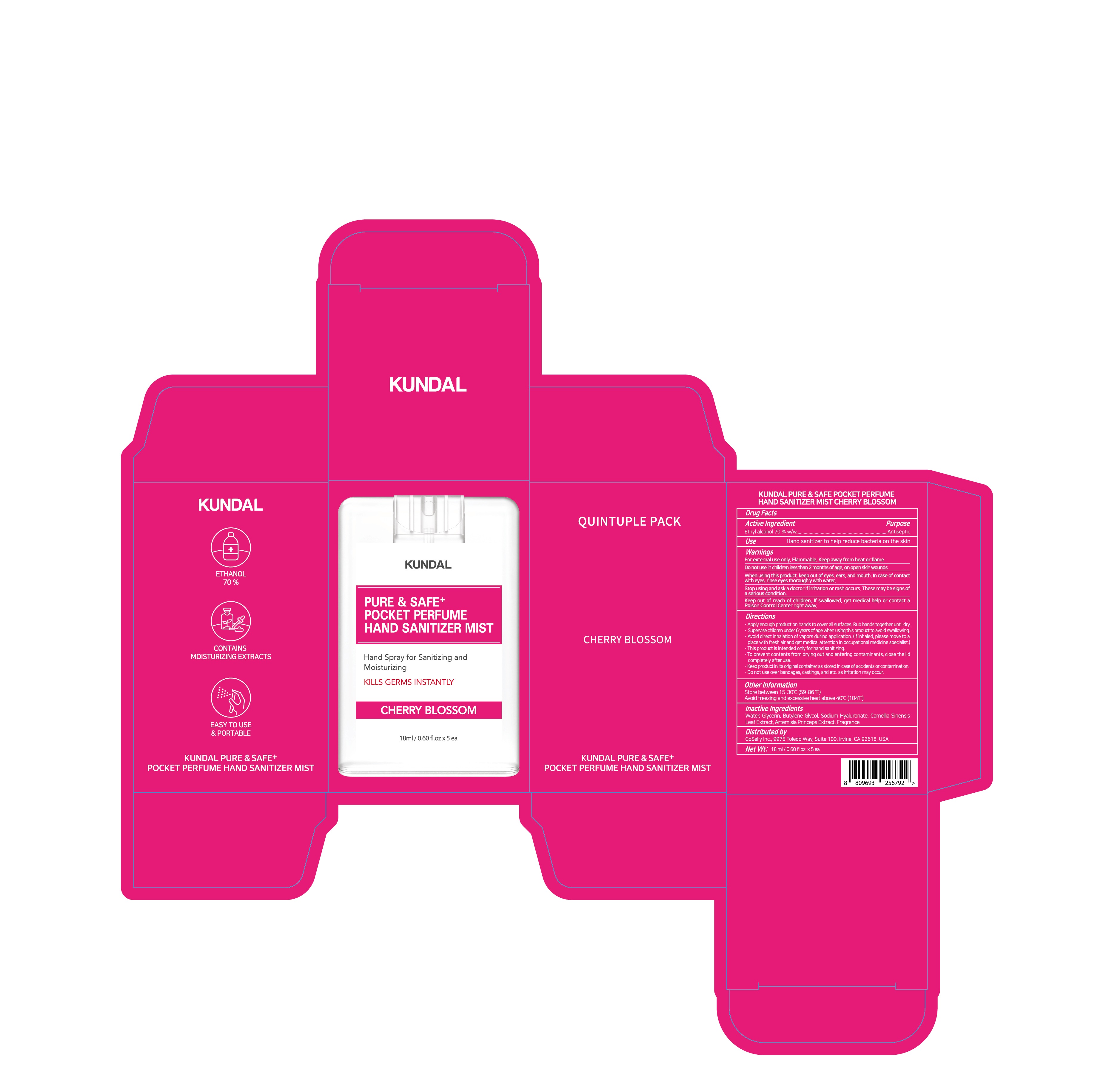 DRUG LABEL: KUNDAL PURE and SAFE POCKET PERFUME HAND SANITIZER MIST CHERRY BLOSSOM
NDC: 74773-0031 | Form: LIQUID
Manufacturer: THESKINFACTORY Co., Ltd.
Category: otc | Type: HUMAN OTC DRUG LABEL
Date: 20201004

ACTIVE INGREDIENTS: ALCOHOL 70 g/100 mL
INACTIVE INGREDIENTS: ARTEMISIA PRINCEPS LEAF; BUTYLENE GLYCOL; GREEN TEA LEAF; WATER; GLYCERIN; HYALURONATE SODIUM

Drug Facts

ACTIVE INGREDIENT

ethanol

INACTIVE INGREDIENT

Water, Butylene Glycol, Glycerin, Sodium Hyaluronate, Camellia Sinensis Leaf Extract, Artemisia Princeps Extract, fragrance

PURPOSE

Antiseptic

KEEP OUT OF REACH OF THE CHILDREN

INDICATIONS AND USAGE

Put enough product in your palm to thoroughly cover your hands.

Rub hands together briskly until dry.

Children under 6 years of age should be supervised when using this product.

WARNINGS

For external use only.

Flammable, keep away from fire or flame.

When using this product keep out of eyes. If contact with eyes occurs, rinse promptly and thoroughly with water.

Stop use and ask a doctor if significant irritation or sensitization develops.

Keep out of reach of children. If swallowed, get medical help or contact a Poison Control Center right away.

DOSAGE AND ADMINISTRATION

For external use only